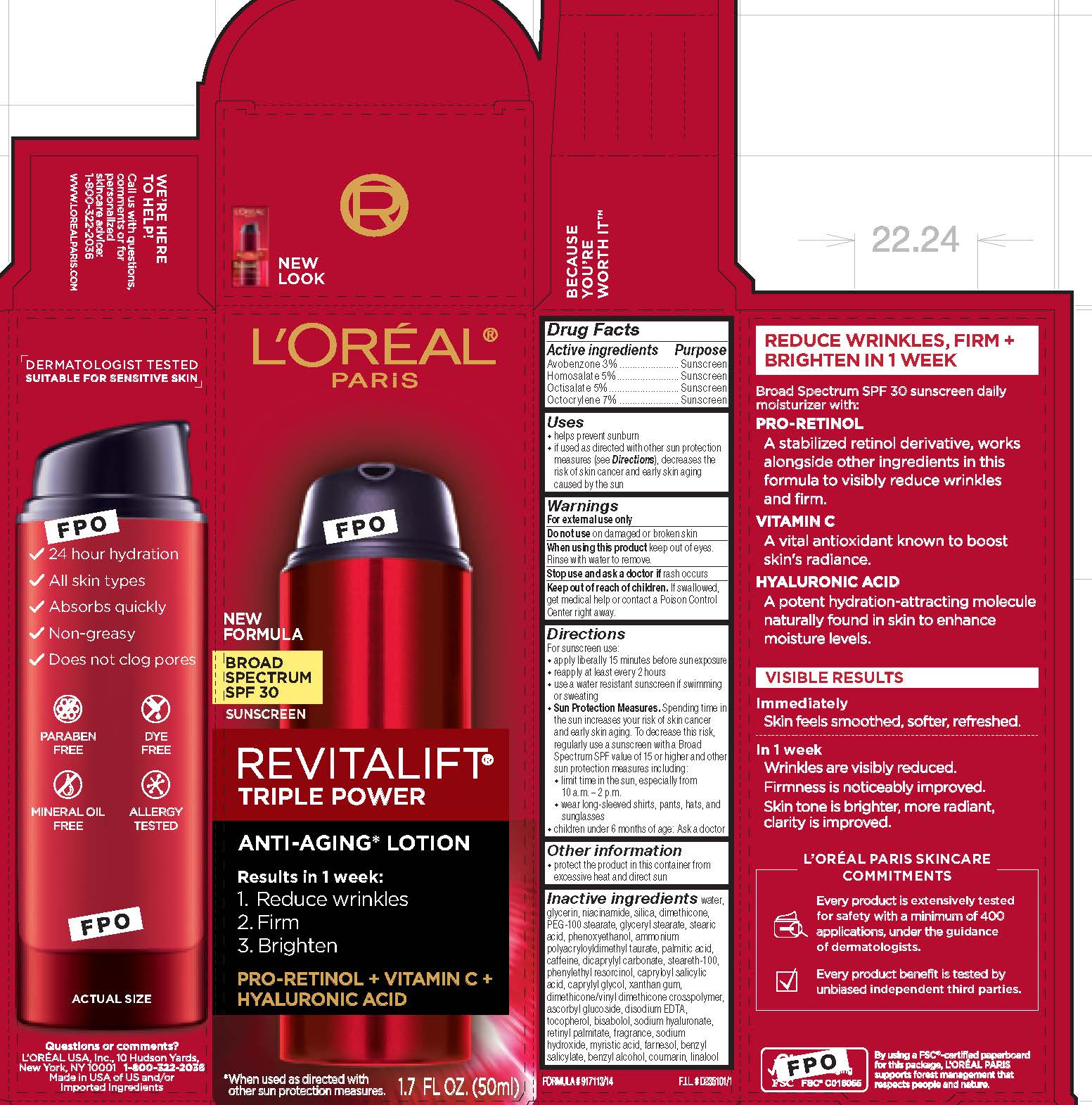 DRUG LABEL: LOreal Paris Revitalift Triple Power Broad Spectrum SPF 30 Sunscreen
NDC: 49967-082 | Form: LOTION
Manufacturer: L'Oreal USA Products Inc
Category: otc | Type: HUMAN OTC DRUG LABEL
Date: 20231229

ACTIVE INGREDIENTS: AVOBENZONE 30 mg/1 mL; HOMOSALATE 50 mg/1 mL; OCTISALATE 50 mg/1 mL; OCTOCRYLENE 70 mg/1 mL
INACTIVE INGREDIENTS: WATER; GLYCERIN; NIACINAMIDE; SILICON DIOXIDE; DIMETHICONE; PEG-100 STEARATE; GLYCERYL MONOSTEARATE; STEARIC ACID; PHENOXYETHANOL; PALMITIC ACID; CAFFEINE; DICAPRYLYL CARBONATE; STEARETH-100; PHENYLETHYL RESORCINOL; CAPRYLOYL SALICYLIC ACID; CAPRYLYL GLYCOL; XANTHAN GUM; ASCORBYL GLUCOSIDE; EDETATE DISODIUM; TOCOPHEROL; LEVOMENOL; HYALURONATE SODIUM; VITAMIN A PALMITATE; SODIUM HYDROXIDE; MYRISTIC ACID; FARNESOL; BENZYL SALICYLATE; BENZYL ALCOHOL; COUMARIN; LINALOOL, (+/-)-

Drug Facts

Active ingredients

Avobenzone 3%

Homosalate 5%

Octisalate 5%

Octocrylene 7%

Purpose

Sunscreen

Uses

- helps prevent sunburn

- if used as directed with other sun protection measures (see Directions), decreases the risk of skin cancer and early skin aging caused by the sun

Warnings

For external use only

Do not use

on damaged or broken skin

When using this product

keep out of eyes. Rinse with water to remove.

Stop use and ask a doctor if

rash occurs

Keep out of reach of children.

If swallowed, get medical help or contact a Poison Control Center right away.

Directions

For sunscreen use:

● apply liberally 15 minutes before sun exposure

● reapply at least every 2 hours

● use a water resistant sunscreen if swimming or sweating

● Sun Protection Measures. Spending time in the sun increases your risk of skin cancer and early skin aging. To decrease this risk, regularly use a sunscreen with a Broad Spectrum SPF value of 15 or higher and other sun protection measures including:

● limit time in the sun, especially from 10 a.m. – 2 p.m.

● wear long-sleeved shirts, pants, hats, and sunglasses

● children under 6 months of age: Ask a doctor

Other information

protect the product in this container from excessive heat and direct sun

Inactive ingredients

water, glycerin, niacinamide, silica, dimethicone, PEG-100 stearate, glyceryl stearate, stearic acid, phenoxyethanol, ammonium polyacryloyldimethyl taurate, palmitic acid, caffeine, dicaprylyl carbonate, steareth-100 , phenylethyl resorcinol, capryloyl salicylic acid, caprylyl glycol, xanthan gum, dimethicone/vinyl dimethicone crosspolymer, ascorbyl glucoside disodium EDTA, tocopherol bisabolol, sodium hyaluronate retinyl palmitate, fragrance , sodium hydroxide, myristic acid, farnesol, benzyl salicylate, benzyl alcohol, coumarin, linalool